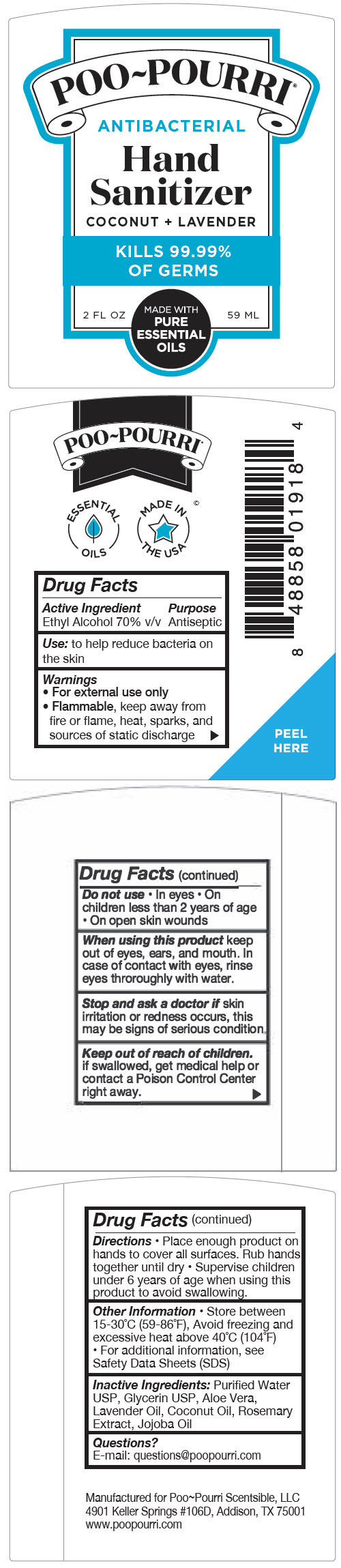 DRUG LABEL: Poo Pourri Antibacterial Hand Sanitizer - Coconut Plus Lavender
NDC: 73754-101 | Form: LIQUID
Manufacturer: Scentsible, LLC
Category: otc | Type: HUMAN OTC DRUG LABEL
Date: 20200714

ACTIVE INGREDIENTS: ALCOHOL 70 mL/100 mL
INACTIVE INGREDIENTS: WATER; Glycerin; ALOE VERA LEAF; Lavender Oil; Coconut Oil; ROSEMARY; JOJOBA OIL

Poo~Pourri® Antibacterial Hand Sanitizer - Coconut + Lavender

Drug Facts

Active Ingredient

Ethyl Alcohol 70% v/v

Purpose

Antiseptic

Use

to help reduce bacteria on the skin

Warnings

- For external use only
- Flammable, keep away from fire or flame, heat, sparks, and sources of static discharge

Do not use

- In eyes
- On children less than 2 years of age
- On open skin wounds

When using this product keep out of eyes, ears, and mouth. In case of contact with eyes, rinse eyes throroughly with water.

STOP USE

Stop and ask a doctor if skin irritation or redness occurs, this may be signs of serious condition.

Keep out of reach of children. if swallowed, get medical help or contact a Polson Control Center right away.

Directions

- Place enough product on hands to cover all surfaces. Rub hands together until dry
- Supervise children under 6 years of age when using this product to avoid swallowing.

Other Information

- Store between 15-30°C (59-86°F), Avoid freezing and excessive heat above 40°C (104°F)
- For additional information, see Safety Data Sheets (SDS)

Inactive Ingredients

Purified Water USP, Glycerin USP, Aloe Vera, Lavender Oil, Coconut Oil, Rosemary Extract, Jojoba Oil

Questions?

E-mail: questions@poopourri.com

PRINCIPAL DISPLAY PANEL - 59 ML Tube Label

POO~POURRI®

ANTIBACTERIAL

Hand
Sanitizer

COCONUT + LAVENDER

KILLS 99.99%
OF GERMS

MADE WITH
PURE
ESSENTIAL
OILS

2 FL OZ
59 ML